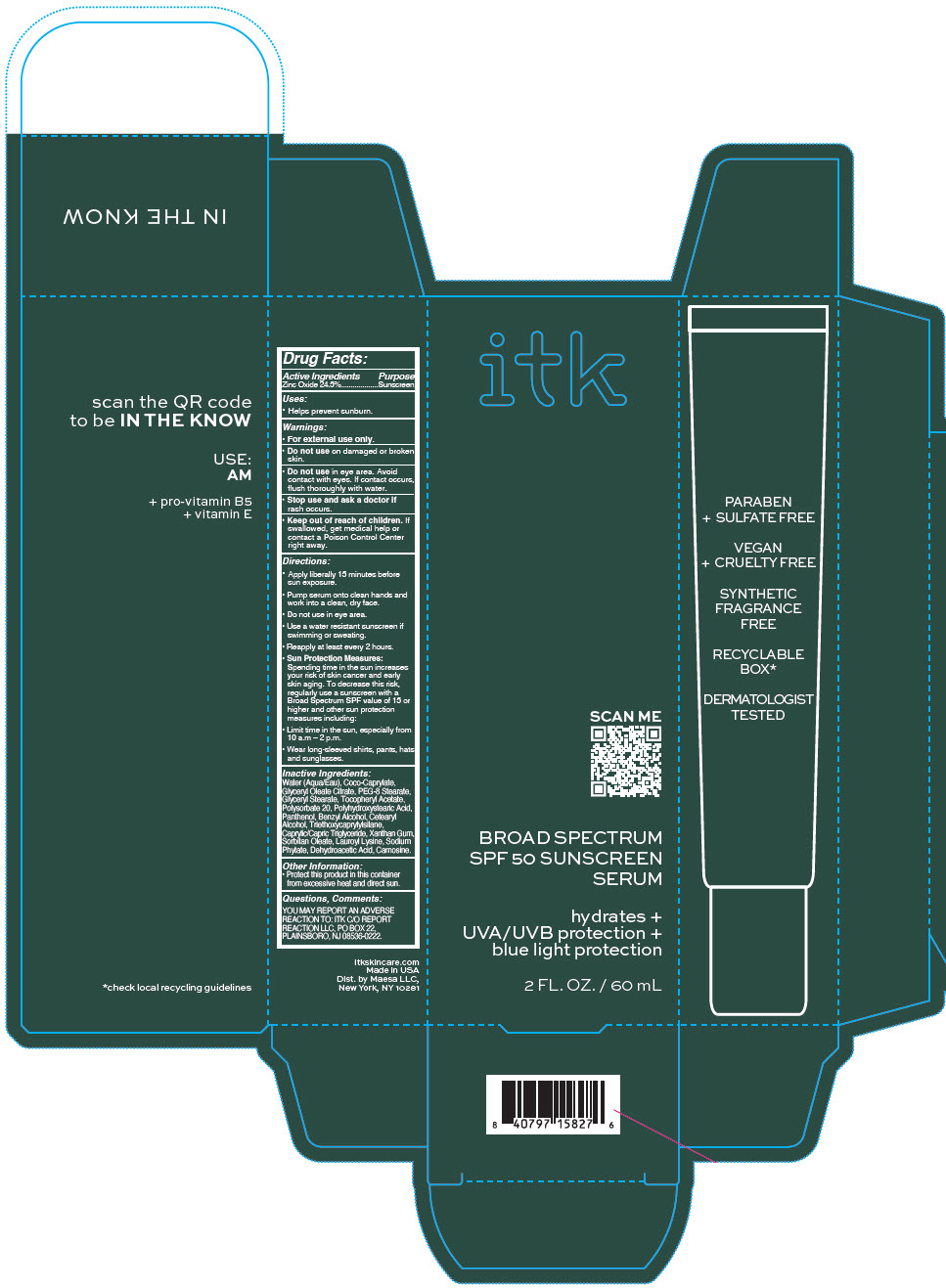 DRUG LABEL: ITK Broad Spectrum SPF 50 Sunscreen Serum
NDC: 71899-066 | Form: LIQUID
Manufacturer: MAESA, LLC.
Category: otc | Type: HUMAN OTC DRUG LABEL
Date: 20220413

ACTIVE INGREDIENTS: Zinc Oxide 24.5 mg/100 mL
INACTIVE INGREDIENTS: Carnosine; ALCOHOL; Coco-Caprylate; GLYCERYL MONOOLEATE CITRATE; PEG-8 Stearate; GLYCERYL MONOSTEARATE; .ALPHA.-TOCOPHEROL ACETATE; Polysorbate 20; POLYHYDROXYSTEARIC ACID (2300 MW); Panthenol; Benzyl Alcohol; CETOSTEARYL ALCOHOL; Triethoxycaprylylsilane; MEDIUM-CHAIN TRIGLYCERIDES; Xanthan Gum; SORBITAN MONOOLEATE; Lauroyl Lysine; PHYTATE SODIUM; Dehydroacetic Acid

ITK Broad Spectrum SPF 50 Sunscreen Serum, 60 ML

Drug Facts:

Active Ingredients

Zinc Oxide 24.5%

Purpose

Sunscreen

Uses

- Helps prevent sunburn.

Warnings

- For external use only.

- Do not use on damaged or broken skin.
- Do not use in eye area. Avoid contact with eyes. If contact occurs, flush thoroughly with water.

- Stop use and ask a doctor if rash occurs.

- Keep out of reach of children. If swallowed, get medical help or contact a Poison Control Center right away.

Directions

- Apply liberally 15 minutes before sun exposure.
- Pump serum onto clean hands and work into a clean, dry face.
- Do not use in eye area.
- Use a water resistant sunscreen if swimming or sweating.
- Reapply at least every 2 hours.
- Sun Protection Measures:
  Spending time in the sun increases your risk of skin cancer and early skin aging. To decrease this risk, regularly use a sunscreen with a Broad Spectrum SPF value of 15 or higher and other sun protection measures including:
  - Limit time in the sun, especially from 10 a.m – 2 p.m.
  - Wear long-sleeved shirts, pants, hats and sunglasses.

Inactive Ingredients

Water (Aqua/Eau), Coco-Caprylate, Glyceryl Oleate Citrate, PEG-8 Stearate, Glyceryl Stearate, Tocopheryl Acetate, Polysorbate 20, Polyhydroxystearic Acid, Panthenol, Benzyl Alcohol, Cetearyl Alcohol, Triethoxycaprylylsilane, Caprylic/Capric Triglyceride, Xanthan Gum, Sorbitan Oleate, Lauroyl Lysine, Sodium Phytate, Dehydroacetic Acid, Carnosine.

Other Information

- Protect this product in this container from excessive heat and direct sun.

Questions, Comments

YOU MAY REPORT AN ADVERSE REACTION TO: ITK C/O REPORT REACTION LLC, PO BOX 22, PLAINSBORO, NJ 08536-0222.

Dist. by Maesa LLC,
New York, NY 10281

PRINCIPAL DISPLAY PANEL - 60 mL Tube Carton

itk

SCAN ME

BROAD SPECTRUM
SPF 50 SUNSCREEN
SERUM

hydrates +
UVA/UVB protection +
blue light protection

2 FL. OZ. / 60 mL